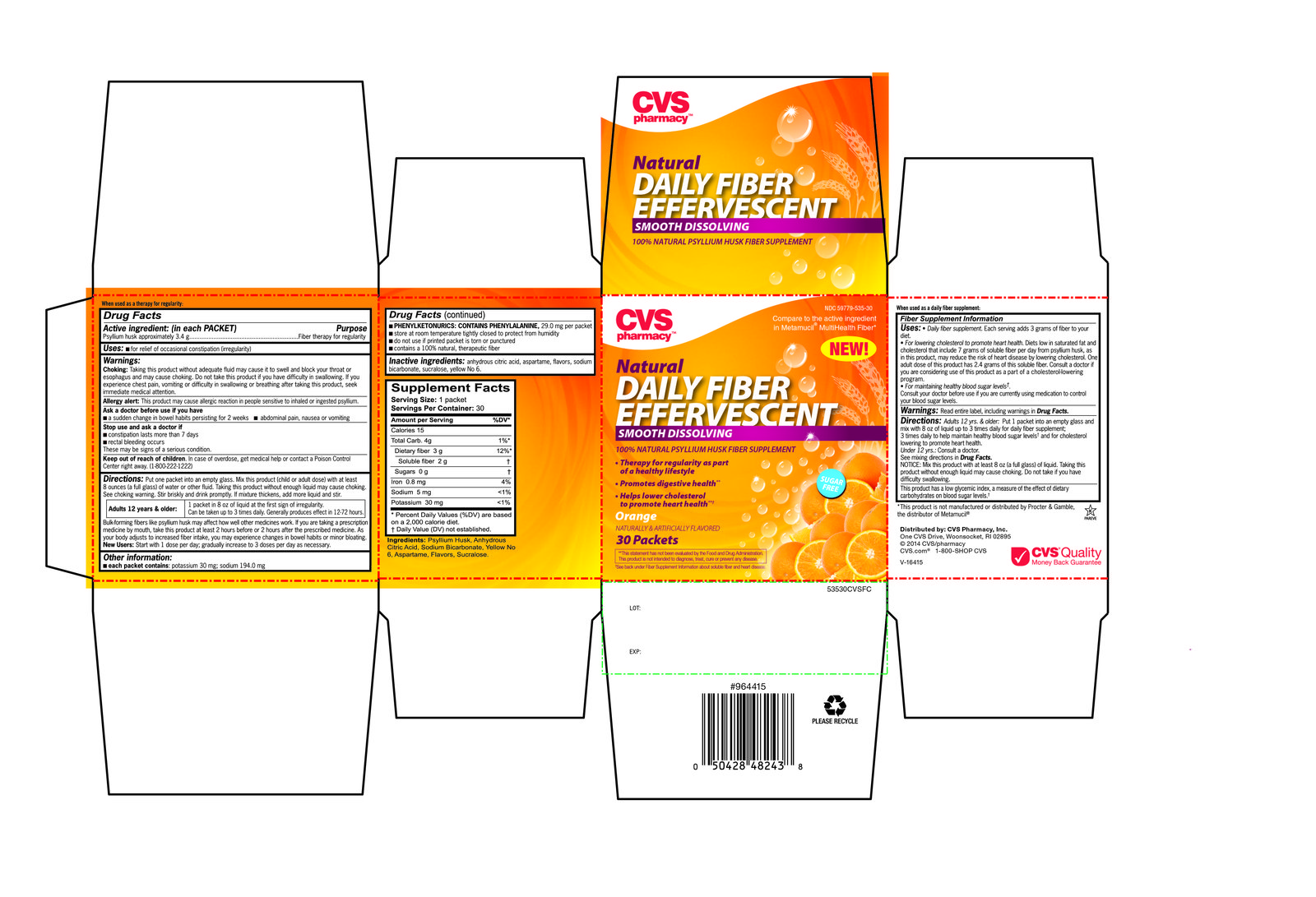 DRUG LABEL: CVS
NDC: 59779-535 | Form: POWDER
Manufacturer: CVS Pharmacy
Category: otc | Type: HUMAN OTC DRUG LABEL
Date: 20130228

ACTIVE INGREDIENTS: Psyllium Husk 3.4 g/5.8 g
INACTIVE INGREDIENTS: aspartame; citric acid monohydrate; FD&C Yellow No. 6; SODIUM BICARBONATE; SUCRALOSE

CVS Natural Fiber Effervescent

Drug Facts

Active ingredient (in each PACKET)

Psyllium husk approximately 3.4 g

Purpose

Fiber therapy for regularity

Uses

- for relief of occasional constipation (irregularity)

Warnings

Choking

Taking this product without adequate fluid may cause it to swell and block your throat or esophagus and may cause choking. Do not take this product if you have difficulty in swallowing. If you experience chest pain, vomiting, or difficulty in swallowing or breathing after taking this product, seek immediate medical attention.

Allergy alert

This product may cause allergic reaction in people sensitive to inhaled or ingested psyllium.

Ask a doctor before use if you have

- a sudden change in bowel habits persisting for 2 weeks
- abdominal pain, nausea or vomiting

Stop use and ask a doctor if

- constipation lasts more than 7 days
- rectal bleeding occurs

These may be signs of a serious condition.

Keep out of reach of children. In case of overdose, get medical help or contact a doctor or a Poison Control Center right away. (1-800-222-1222)

Directions

Put one packet into an empty glass. Mix this product (child or adult dose) with at least 8 ounces (a full glass) of water or other fluid. Taking this product without enough liquid may cause choking. See choking warning. Stir briskly and drink promptly. If mixture thickens, add more liquid and stir.

Adults 12 yrs. & older: | 1 packet in 8 oz of liquid at the first sign of irregularity. Can be taken up to 3 times daily. Generally produces effect in 12 – 72 hours.

Bulk forming fibers, like psyllium husk may affect how well other medicines work. If you are taking a prescription medicine by mouth, take this product at least 2 hours before or 2 hours after the prescribed medicine. As your body adjusts to increased fiber intake, you may experience changes in bowel habits or minor bloating.

New Users

Start with 1 dose per day; gradually increase to 3 doses per day as necessary.

Other information

- each packet contains: potassium 30 mg; sodium 194.0 mg
- PHENYLKETONURICS: CONTAINS PHENYLALANINE, 29.0 mg per teaspoon
- store at room temperature tightly closed to protect from humidity
- do not use if printed package is torn or punctured
- contains a 100% natural, therapeutic fiber

Inactive ingredients

anhydrous citric acid, aspartame, flavors, sodium bicarbonate, sucralose, yellow no 6.

Distributed By: CVS Pharmacy, Inc.

One CVS Drive, Woonsocket RI 02895

CVS.com

1-800-SHOP CVS

PRINCIPAL DISPLAY PANEL

Natural Daily Fiber Effervescent

Smooth Dissolving
100% Natural Psyllium Husk Fiber Supplement

Compare to the active ingredient in Metamucil® MultiHealth Fiber

Sugar Free

Therapy for regularity as part of a healthy lifestyle

Promotes digestive health

Helps lower cholesterol to promote heart health

Orange

Naturally and Artificially Flavored

30 Packets